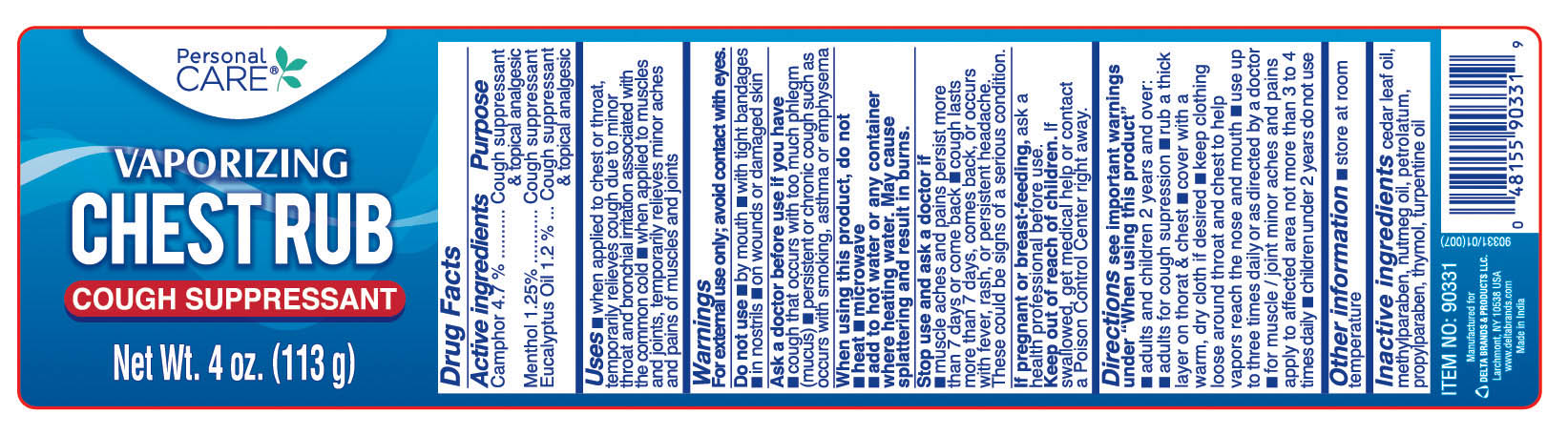 DRUG LABEL: Personal CARE
NDC: 72133-100 | Form: OINTMENT
Manufacturer: Delta Brands & Products LLC
Category: otc | Type: HUMAN OTC DRUG LABEL
Date: 20180413

ACTIVE INGREDIENTS: CAMPHOR (SYNTHETIC) 4.7 g/100 g; MENTHOL 1.25 g/100 g; EUCALYPTUS OIL 1.2 g/100 g
INACTIVE INGREDIENTS: CEDAR LEAF OIL; NUTMEG; METHYLPARABEN; PETROLATUM; THYMOL; TURPENTINE; PROPYLPARABEN

Active ingredients

Camphor 4.7%

Menthol 1.25%

Eucalyptus Oil 1.2%

Purpose

Cough suppressant & topical analgesic

Cough suppressant

Cough suppressant & topical anlagesic

Uses

■ when applied to chest or throat temporarily relieves cough due to minor throat and bronchial irritation associated with the common cold ■ when applied to muscles and joints, temporarily relieves minor aches and pains of muscles and joints

Warnings

For external use only; avoid contact with eyes.

Do not use

■ by mouth ■ with tight bandages ■ in nostrils ■ on wounds or damaged skin

Ask a doctor before use if you have

■ cough that occurs with too much phlegm (mucus) ■ persistent or chronic cough such as occurs with emoking, asthma or emphysema

When using this product, do not

■heat ■ microwave ■ add to hot water or any container where heating water. May cause splattering and result in burns

Stop use and ask a doctor if

■ muscle aches and pains persist for more than 7 days or come back, ■ cough lasts more than 7 days comes back or occurs with fever, rash or persistent headache. These could be signs of a serious condition. If pregnant or breast-feeding, ask a health professional before use

Keep out of reach of children

If swallowed, get medical help or contact a Poison Control Center iright away.

Directions

see important warnings under "When using this product"

■ adults and children 2 years and over: ■ adults for cough supression ■ rub a thick layer on throat & chest. ■ cover with a wrm dry cloth if desired ■ keep clothing loose around throat and chest to help vapors reach the nose and mouth ■ use up to three times daily or as directed by a doctor ■ for muscle joint minor aches and pains apply to affected area not more than 3 to 4 times daily ■ children under 2 years do not use

Other information

■ store at room temperature

Inactive ingredients

cedar leaf oil, methylparaben, nutmeg oil, petrolatum, propylparaben,thymol, turpentine oil